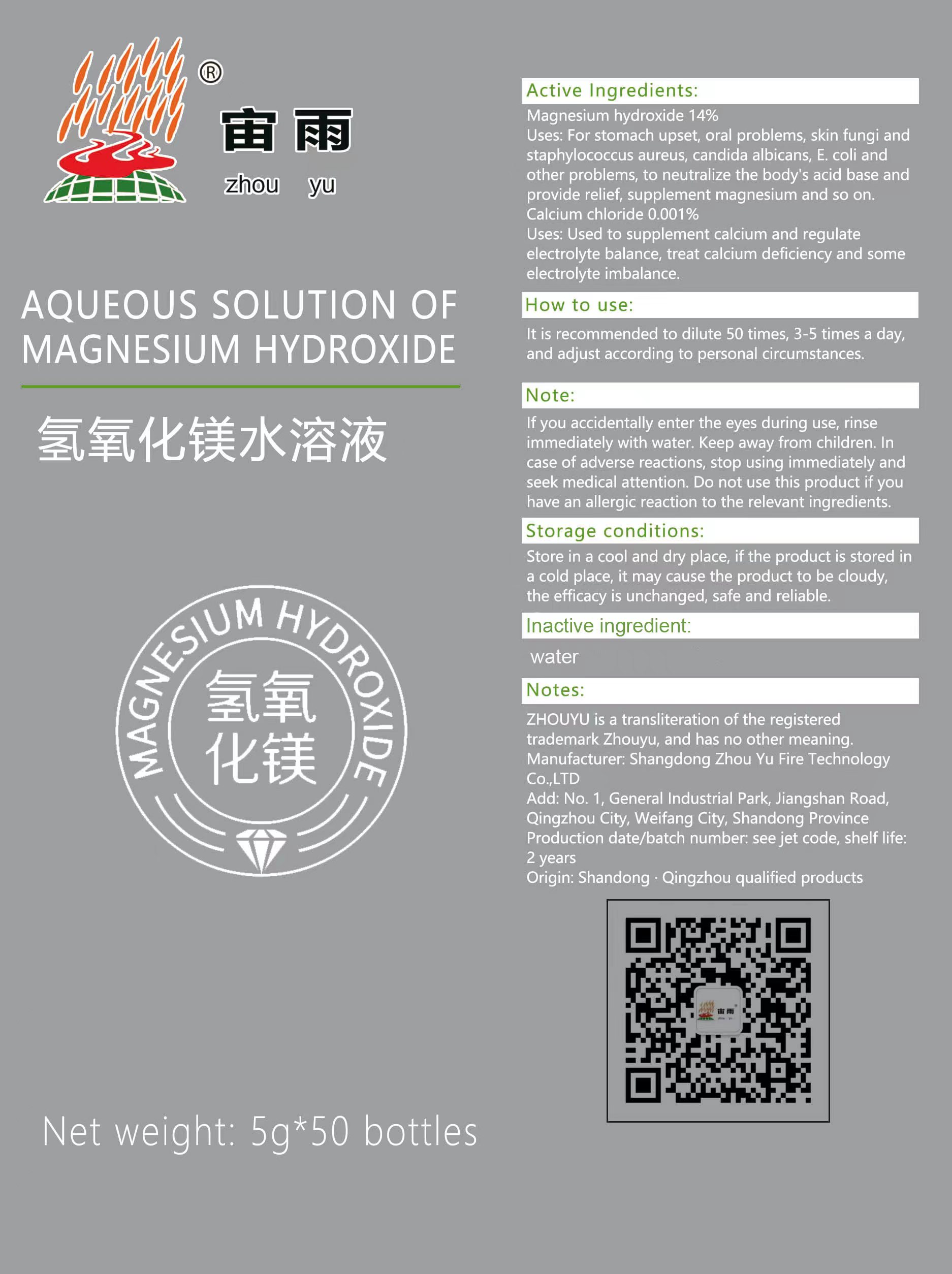 DRUG LABEL: MAGNESIUM HYDROXIDE
NDC: 83674-001 | Form: LIQUID
Manufacturer: Shandong Zhouyu Fire Technology Co.,Ltd
Category: otc | Type: HUMAN OTC DRUG LABEL
Date: 20230908

ACTIVE INGREDIENTS: MAGNESIUM HYDROXIDE 14 g/100 g; CALCIUM CHLORIDE 0.001 g/100 g
INACTIVE INGREDIENTS: WATER

ACTIVE INGREDIENT

Magnesium hydroxide 14％

calcium chloride 0.001％

PURPOSE

For stomach upset , oral problems , skin fungi and staphylococcus aureus , candida albicans , E coli andother problems , to neutralize the body's acid base and provide relief , supplement magnesium and so on.

Used to supplement calcium and regulate electrolyte balance , treat calcium deficiency and some electrolyte imbalance

Uses

For stomach upset , oral problems , skin fungi andstaphylococcus aureus , candida albicans , E coli andother problems , to neutralize the body's acid base andprovide relief , supplement magnesium and so on.

Used to supplement calcium and regulateelectrolyte balance , treat calcium deficiency and someelectrolyte imbalance

DO NOT USE

If you accidentally enter the eyes during use , rinse immediately with water . Keep away from children . In case of adverse reactions , stop using immediately and seek medical attention . Do not use this product if you have an allergic reaction to the relevant ingredients

WHEN USING

It is recommended to dilute 50 times , 3-5 times a day ,and adjust according to personal circumstances

STOP USE

If you accidentally enter the eyes during use , rinse immediately with water . Keep away from children . In case of adverse reactions , stop using immediately and seek medical attention . Do not use this product if you have an allergic reaction to the relevant ingredients

Keep away from children

DOSAGE AND ADMINISTRATION

It is recommended to dilute 50 times , 3-5 times a day ,and adjust according to personal circumstances

Storage conditions

Store in a cool and dry place , if the product is stored ina cold place , it may cause the product to be cloudythe efficacy is unchanged , safe and reliable

inactive ingredient

water